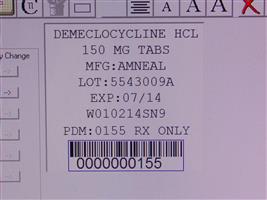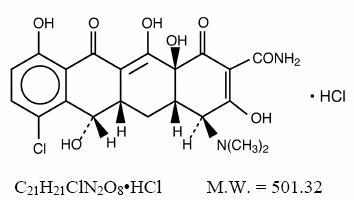 DRUG LABEL: Demeclocycline Hydrochloride
                                    
NDC: 68151-0155 | Form: TABLET
Manufacturer: Carilion Materials Management
Category: prescription | Type: HUMAN PRESCRIPTION DRUG LABEL
Date: 20100401

ACTIVE INGREDIENTS: DEMECLOCYCLINE HYDROCHLORIDE 150 mg/1 1
INACTIVE INGREDIENTS: ALGINIC ACID; STARCH, CORN; ETHYLCELLULOSES; FD&C RED NO. 40; HYPROMELLOSES; MAGNESIUM STEARATE; CELLULOSE, MICROCRYSTALLINE; POLYETHYLENE GLYCOLS; POLYVINYL ALCOHOL; SODIUM LAURYL SULFATE; TALC; TITANIUM DIOXIDE; D&C RED NO. 27

DEMECLOCYCLINE HYDROCHLORIDE Tablets, USP
(Film Coated)

Full Prescribing Information

To reduce the development of drug-resistant bacteria and maintain the effectiveness of demeclocycline hydrochloride tablets and other antibacterial drugs, demeclocycline hydrochloride tablets should be used only to treat or prevent infections that are proven or strongly suspected to be caused by bacteria.

DESCRIPTION

Demeclocycline hydrochloride is an antibiotic isolated from a mutant strain of . Chemically it is 7-Chloro-4-(dimethylamino)-1,4,4a,5,5a,6,11,12a-octahydro-3,6,10,12, 12a-pentahydroxy-1,11-dioxo-2-naphthacenecarboxamide monohydrochloride. Its structural formula is: Streptomyces aureofaciens

Demeclocycline hydrochloride film coated tablets for oral administration contain 150 mg or 300 mg of demeclocycline hydrochloride and the following inactive ingredients: alginic acid, corn starch, ethylcellulose, FD&C Red 40 aluminum lake, hypromellose, magnesium stearate, microcrystalline cellulose, polyethylene glycol, polyvinyl alcohol, sodium lauryl sulfate, talc and titanium dioxide. In addition, the 150 mg tablet contains D&C Red 27 aluminum lake.

CLINICAL PHARMACOLOGY

The absorption of demeclocycline is slower than that of tetracycline. The time to reach the peak concentration is about 4 hours. After a 150 mg oral dose of demeclocycline tablet, the mean concentrations at 1 hour and 3 hours are 0.46 and 1.22 mcg/mL (n = 6), respectively. The serum half-life ranges between 10 and 16 hours. Pharmacokinetics

When demeclocycline hydrochloride is given concomitantly with some dairy products, or antacids containing aluminum, calcium, or magnesium, the extent of absorption is reduced by more than 50%.

Demeclocycline hydrochloride penetrates well into various body fluids and tissues. The percent of demeclocycline hydrochloride bound to plasma protein is about 40% using a dialysis equilibrium method and 90% using an ultra-filtration method. Demeclocycline hydrochloride, like other tetracyclines, is concentrated in the liver and excreted into the bile where it is found in much higher concentrations than in the blood. The rate of demeclocycline hydrochloride renal clearance (35 mL/min/1.73 m) is less than half that of tetracycline. Following a single 150 mg dose of demeclocycline hydrochloride in normal volunteers, 44% (n = 8) was excreted in urine and 13% and 46%, respectively, were excreted in feces in two patients within 96 hours as active drug.^2

The tetracyclines are primarily bacteriostatic and are thought to exert their antimicrobial effect by the inhibition of protein synthesis. The tetracyclines, including demeclocycline, have a similar antimicrobial spectrum of activity against a wide range of gram-negative and gram-positive organisms. Cross-resistance of these organisms to tetracyclines is common. Microbiology

Demeclocycline has been shown to be active against most strains of the following microorganisms, both and in clinical infections as described in the section. in vitro INDICATIONS AND USAGE

AEROBIC GRAM-POSITIVE MICROORGANISMS:
Bacillus anthracis | Listeria monocytogenes
Staphylococcus aureus | Streptococcus pneumoniae

AEROBIC GRAM-NEGATIVE MICROORGANISMS:
Bartonella bacilliformis | species Brucella
Calymmatobacterium granulomatis | Campylobacter fetus
Francisella tularensis | Haemophilus ducreyi
Haemophilus influenzae | Neisseria gonorrhoeae
Vibrio cholerae | Yersinia pestis

Because many strains of the following groups of gram-negative microorganisms have been shown to be resistant to tetracyclines, culture and susceptibility testing are especially recommended:

species Acinetobacter | Enterobacter aerogenes
Escherichia coli | species Klebsiella
Shigella species

OTHER MICROORGANISMS:
Actinomyces israelii | Borrelia recurrentis
Chlamydia psittaci | Chlamydia trachomatis
species Clostridium | species Entamoeba
Fusobacterium fusiforme | Mycoplasma pneumoniae
Propionibacterium acnes | Rickettsiae
subspecies Treponema pallidumpallidum | subspecies Treponema pallidumpertenue
Ureaplasma urealyticum

Susceptibility Tests

Dilution Techniques

Quantitative methods are used to determine antimicrobial minimum inhibitory concentrations (MICs). These MICs provide estimates of the susceptibility of bacteria to antimicrobial compounds. The MICs should be determined using a standardized procedure. Standardized procedures are based on a dilution method (broth or agar) or equivalent with standardized inoculum concentrations and standardized concentrations of demeclocycline hydrochloride or tetracycline powder. The MIC values should be interpreted according to the following criteria:^1

For organisms other than species, and species: Haemophilus Neisseria gonorrhoeae Streptococcus^2

MIC (mcg/mL) | Interpretation
≤ 4 | Susceptible (S)
8 | Intermediate (I)
≥16 | Resistant (R)

For and species: Haemophilus Streptococcus^2

MIC (mcg/mL) | Interpretation
≤ 2 | Susceptible (S)
4 | Intermediate (I)
≥8 | Resistant (R)

For : Neisseria gonorrhoeae^2

MIC (mcg/mL) | Interpretation
≤ 0.25 | Susceptible (S)
0.5 to 1 | Intermediate (I)
≥2 | Resistant (R)

A report of “Susceptible” indicates that the pathogen is likely to be inhibited by usually achievable concentrations of the antimicrobial compound in blood. A report of “Intermediate” indicates that the result should be considered equivocal, and, if the microorganism is not fully susceptible to alternative, clinically feasible drugs, the test should be repeated. This category implies possible clinical applicability in body sites where the drug is physiologically concentrated or in situations where high dosage of drug can be used. This category also provides a buffer zone which prevents small uncontrolled technical factors from causing major discrepancies in interpretation. A report of “Resistant” indicates that usually achievable concentrations of the antimicrobial compound in the blood are unlikely to be inhibitory and that other therapy should be selected.

Standardized susceptibility test procedures require the use of laboratory control microorganisms to control the technical aspects of the laboratory procedures. Standard demeclocycline or tetracycline powder should provide the following MIC values:^2

Microorganism | MIC (mcg/mL) | Microorganism | MIC (mcg/mL)
ATCC 25922 E.coli, | 1 to 4 | ATCC 49226 N. gonorrhoeae, | 0.25 to 1
ATCC 29212 E. faecalis, | 8 to 32 | ATCC 29213 S. aureus, | 0.25 to 1
ATCC 49247 H. influenzae, | 4 to 32 | ATCC 49619 S. pneumoniae, | 0.12 to 0.5

Quantitative methods that require measurement of zone diameters also provide reproducible estimates of the susceptibility of bacteria to antimicrobial compounds. One such standardized procedure requires the use of standardized inoculum concentrations. This procedure uses paper disks impregnated with 30-mcg tetracycline (as a class disk) or a 30-mcg demeclocycline hydrochloride disk to test the susceptibility of microorganisms to demeclocycline. Reports from the laboratory providing results of the standard single-disk susceptibility test with either a 30-mcg tetracycline-class disk or a 30-mcg demeclocycline disk should be interpreted according to the following criteria: For organisms other than species, and species: Diffusion Techniques
^2
Haemophilus Neisseria gonorrhoeae Streptococcus^2

Zone Diameter (mm) | Interpretation
≥ 19 | Susceptible (S)
15 to 18 | Intermediate (I)
≤ 14 | Resistant (R)

For species: Haemophilus^2

Zone Diameter (mm) | Interpretation
≥ 29 | Susceptible (S)
26 to 28 | Intermediate (I)
≤ 25 | Resistant (R)

For : N. gonorrhoeae^2

Zone Diameter (mm) | Interpretation
≥ 38 | Susceptible (S)
31 to 37 | Intermediate (I)
≤ 30 | Resistant (R)

For species: Streptococcus^2

Zone Diameter (mm) | Interpretation
≥ 23 | Susceptible (S)
19 to 22 | Intermediate (I)
≤ 18 | Resistant (R)

Interpretation should be as stated above for results using dilution techniques. Interpretation involves correlation of the diameter obtained in the disk test with the MIC for demeclocycline hydrochloride or tetracycline.

As with standardized dilution techniques, diffusion methods require the use of laboratory control microorganisms to control the technical aspects of the laboratory procedures. For the diffusion technique, the 30-mcg demeclocycline hydrochloride disk or the 30-mcg tetracycline-class disk should provide the following zone diameters in these laboratory test quality control strains:
^2

Microorganism | Zone Diameter (mm)
, ATCC 25922 E. coli | 18 to 25
ATCC 49247 H. influenzae, | 14 to 22
, ATCC 49226 N. gonorrhoeae | 30 to 42
, ATCC 25923 S. aureus | 24 to 30
, ATCC 49619 S. pneumoniae | 27 to 31

INDICATIONS & USAGE

To reduce the development of drug-resistant bacteria and maintain the effectiveness of demeclocycline hydrochloride tablets and other antibacterial drugs, demeclocycline hydrochloride tablets should be used only to treat or prevent infections that are proven or strongly suspected to be caused by susceptible bacteria. When culture and susceptibility information are available, they should be considered in selecting or modifying antibacterial therapy. In the absence of such data, local epidemiology and susceptibility patterns may contribute to the empiric selection of therapy. Demeclocycline hydrochloride is indicated in the treatment of infections caused by susceptible strains of the designated microorganisms in the conditions below:

Rocky Mountain spotted fever, typhus fever and the typhus group, Q fever, rickettsialpox, and tick fevers caused by rickettsiae; Respiratory tract infections caused by ; Lymphogranuloma venereum due to ; Psittacosis (Ornithosis) due to ; Trachoma due to , although the infectious agent is not always eliminated, as judged by immunofluorescence; Inclusion conjunctivitis caused by ; Nongonococcal urethritis in adults caused by or ; Relapsing fever due to ; Chancroid caused by ; Plague due to ; Tularemia due to ; Cholera caused by ; Campylobacter fetus infections caused by ; Brucellosis due to species (in conjunction with streptomycin); Bartonellosis due to ; Granuloma inguinale caused by ; Demeclocycline hydrochloride is indicated for treatment of infections caused by the following gram-negative microorganisms, when bacteriologic testing indicates appropriate susceptibility to the drug: ; ; species; species; Respiratory tract infections caused by ; Respiratory tract and urinary tract infections caused by species. Demeclocycline hydrochloride is indicated for treatment of infections caused by the following gram-positive microorganisms, when bacteriologic testing indicates appropriate susceptibility to the drug: Upper respiratory infections caused by pneumoniae; Skin and skin structure infections caused by . (Note: Tetracyclines, including demeclocycline, are not the drugs of choice in the treatment of any type of staphylococcal infection.) When penicillin is contraindicated, tetracyclines, including demeclocycline hydrochloride, are alternative drugs in the treatment of the following infections: Uncomplicated urethritis in men due to , and for the treatment of other uncomplicated gonococcal infections; Infections in women caused by ; Syphilis caused by subspecies ; Yaws caused by subspecies ; Listeriosis due to ; Anthrax due to ; Vincent’s infection caused by ; Actinomycosis caused by ; Clostridial diseases caused by species. In acute intestinal amebiasis, demeclocycline hydrochloride may be a useful adjunct to amebicides. In severe acne, demeclocycline hydrochloride may be a useful adjunctive therapy.
Mycoplasma pneumoniae
Chlamydia trachomatis
Chlamydia psittaci
Chlamydia trachomatis
Chlamydia trachomatis
Ureaplasma urealyticum Chlamydia trachomatis
Borrelia recurrentis
Haemophilus ducreyi
Yersinia pestis
Francisella tularensis
Vibrio cholerae
Campylobacter fetus
Brucella
Bartonella bacilliformis
Calymmatobacterium granulomatis
Escherichia coli
Enterobacter aerogenes
Shigella
Acinetobacter
Haemophilus influenzae
Klebsiella
Streptococcus
Staphylococcus aureus
Neisseria gonorrhoeae
Neisseria gonorrhoeae
Treponema pallidumpallidum
Treponema pallidumpertenue
Listeria monocytogenes
Bacillus anthracis
Fusobacterium fusiforme
Actinomyces israelii
Clostridium

CONTRAINDICATIONS

This drug is contraindicated in persons who have shown hypersensitivity to any of the tetracyclines or any of the components of the product formulation.

WARNINGS

DEMECLOCYCLINE HYDROCHLORIDE, LIKE OTHER TETRACYCLINE-CLASS ANTIBIOTICS, CAN CAUSE FETAL HARM WHEN ADMINISTERED TO A PREGNANT WOMAN. IF ANY TETRACYCLINE IS USED DURING PREGNANCY, OR IF THE PATIENT BECOMES PREGNANT WHILE TAKING THESE DRUGS, THE PATIENT SHOULD BE APPRISED OF THE POTENTIAL HAZARD TO THE FETUS.

THE USE OF DRUGS OF THE TETRACYCLINE CLASS DURING TOOTH DEVELOPMENT (LAST HALF OF PREGNANCY, INFANCY AND CHILDHOOD TO THE AGE OF 8 YEARS) MAY CAUSE PERMANENT DISCOLORATION OF THE TEETH (YELLOW-GRAY-BROWN). This adverse reaction is more common during long-term use of the drugs but has been observed following repeated short-term courses. Enamel hypoplasia has also been reported. TETRACYCLINE DRUGS, THEREFORE, SHOULD NOT BE USED DURING TOOTH DEVELOPMENT UNLESS OTHER DRUGS ARE NOT LIKELY TO BE EFFECTIVE OR ARE CONTRAINDICATED.

All tetracyclines form a stable calcium complex in any bone-forming tissue. A decrease in fibula growth rate has been observed in premature human infants given oral tetracycline in doses of 25 mg/kg every six hours. This reaction was shown to be reversible when the drug was discontinued.

Results of animal studies indicate that tetracyclines cross the placenta, are found in fetal tissues, and can have toxic effects on the developing fetus (often related to retardation of skeletal development). Evidence of embryotoxicity has also been noted in animals treated early in pregnancy.

The anti-anabolic action of the tetracyclines may cause an increase in BUN. While this is not a problem in those with normal renal function, in patients with significantly impaired function, higher serum levels of tetracycline may lead to azotemia, hyperphosphatemia, and acidosis.

If renal impairment exists, even usual oral or parenteral doses may lead to excessive systemic accumulation of the drug and possible liver toxicity. Under such conditions, lower than usual total doses are indicated and, if therapy is prolonged, serum level determinations of the drug may be advisable.

Photosensitivity manifested by an exaggerated sunburn reaction has been observed in some individuals taking tetracyclines. Phototoxic reactions can occur in individuals taking demeclocycline, and are characterized by severe burns of exposed surfaces resulting from direct exposure of patients to sunlight during therapy with moderate or large doses of demeclocycline. Patients apt to be exposed to direct sunlight or ultraviolet light should be advised that this reaction can occur, and treatment should be discontinued at the first evidence of erythema of the skin.

Administration of demeclocycline hydrochloride has resulted in appearance of the diabetes insipidus syndrome (polyuria, polydipsia and weakness) in some patients on long-term therapy. The syndrome has been shown to be nephrogenic, dose-dependent and reversible on discontinuance of therapy.

Patients who are experiencing central nervous system symptoms associated with demeclocycline therapy, should be cautioned about driving vehicles or using hazardous machinery while on demeclocycline therapy.

PRECAUTIONS

Prescribing demeclocycline hydrochloride tablets in the absence of a proven or strongly suspected bacterial infection or a prophylactic indication is unlikely to provide benefit to the patient and increase the risk of the development of drug-resistant bacteria. General

Pseudotumor cerebri (benign intracranial hypertension) in adults has been associated with the use of tetracyclines. The usual clinical manifestations are headache and blurred vision. Bulging fontanels have been associated with the use of tetracyclines in infants. While both of these conditions and related symptoms usually resolve soon after discontinuation of the tetracycline, the possibility for permanent sequelae exists.

As with other antibiotic preparations, use of this drug may result in overgrowth of nonsusceptible organisms, including fungi. If superinfection occurs, the antibiotic should be discontinued and appropriate therapy should be instituted.

Incision and drainage or other surgical procedures should be performed in conjunction with antibiotic therapy, when indicated.

Patients should be counseled that antibacterial drugs including demeclocycline hydrochloride tablets should only be used to treat bacterial infections. They do not treat viral infections (e.g. the common cold). When demeclocycline hydrochloride tablets are prescribed to treat bacterial infection, patients should be told that although it is common to fell better early in the course of therapy, the medication should be taken exactly as directed. Skipping doses or not completing the full course of therapy (1) decrease the effectiveness of the immediate treatment and (2) increase the likelihood that bacteria will develop resistance and will not be treatable by demeclocycline hydrochloride tablets or other antibacterial drugs in the future. Information for Patients

Photosensitivity manifested by an exaggerated sunburn reaction has been observed in some individuals taking tetracyclines. Patients apt to be exposed to direct sunlight or ultraviolet light should be advised that this reaction can occur with tetracycline drugs, and treatment should be discontinued at the first evidence of skin erythema.

Concurrent use of tetracyclines with oral contraceptives may render oral contraceptives less effective. (See .) Drug Interactions

Patients should be informed that demeclocycline hydrochloride tablets should be taken at least 1 hour before meals or 2 hours after meals. (See .) DOSAGE AND ADMINISTRATION

Unused supplies of tetracycline antibiotics should be discarded by the expiration date.

Patients who are experiencing headache, dizziness, light-headedness, vertigo, or blurred vision while on demeclocycline therapy, should be cautioned about driving vehicles or using hazardous machinery while receiving demeclocycline therapy. (See .) WARNINGS

Laboratory Tests

In venereal diseases when coexistent syphilis is suspected, darkfield examination should be done before treatment is started and the blood serology repeated monthly for at least 4 months.

In long-term therapy, periodic laboratory evaluation of organ systems, including hematopoietic, renal, and hepatic, should be performed.

All patients with gonorrhea should have a serologic test for syphilis at the time of diagnosis. Patients treated with demeclocycline hydrochloride should have a follow-up serologic test for syphilis after 3 months.

Drug Interactions

Because tetracyclines have been shown to depress plasma prothrombin activity, patients who are on anticoagulant therapy may require downward adjustment of their anticoagulant dosage.

Since bacteriostatic drugs may interfere with the bactericidal action of penicillins, it is advisable to avoid giving tetracycline-class drugs in conjunction with penicillin.

Concurrent use of tetracyclines with oral contraceptives may render oral contraceptives less effective.

The concurrent use of tetracyclines and methoxyflurane has been reported to result in fatal renal toxicity.

Absorption of tetracyclines is impaired by antacids containing aluminum, calcium or magnesium, and by iron-containing preparations.

Long-term studies in animals to evaluate carcinogenic potential of demeclocycline hydrochloride have not been conducted. However, there has been evidence of oncogenic activity in rats in studies with the related antibiotics oxytetracycline (adrenal and pituitary tumors) and minocycline (thyroid tumors). Carcinogenesis, Mutagenesis, Impairment of Fertility

Although mutagenicity studies of demeclocycline hydrochloride have not been conducted, positive results in mammalian cell assays (i.e., mouse lymphoma and Chinese hamster lung cells) have been reported for related antibiotics (tetracycline hydrochloride and oxytetracycline). (See and .) in vitro WARNINGSANIMAL PHARMACOLOGY AND ANIMAL TOXICOLOGY

Demeclocycline hydrochloride had no effect on fertility when administered in the diet to male and female rats at a daily intake of 45 times the human dose.

. (See .) Pregnancy
Teratogenic effects. Pregnancy Category DWARNINGS

Results of animal studies indicate that tetracyclines cross the placenta, are found in fetal tissues, and can have toxic effects on the developing fetus (often related to retardation of skeletal development). Evidence of embryotoxicity has been noted in animals treated early in pregnancy.

(See .) Nonteratogenic effects. WARNINGS

The effect of tetracyclines on labor and delivery is unknown. Labor and Delivery

Tetracyclines are excreted in human milk. Because of the potential for serious adverse reactions in nursing infants from the tetracyclines, a decision should be made whether to discontinue nursing or discontinue the drug, taking into account the importance of the drug to the mother. Nursing Mothers

(See .) WARNINGS

Not for use in patients younger than eight years of age. See , (subsection) and . Pediatric Use
WARNINGSPRECAUTIONSGeneral DOSAGE AND ADMINISTRATION

ADVERSE REACTIONS

The following reactions have been reported in patients receiving tetracyclines:

Gastrointestinal: Anorexia, nausea, vomiting, diarrhea, glossitis, dysphagia, enterocolitis, pancreatitis, and inflammatory lesions (with monilial overgrowth) in the anogenital region, increases in liver enzymes, and hepatic toxicity has been reported rarely.

Rarely, hepatitis and liver failure have been reported. These reactions have been caused by both the oral and parenteral administration of tetracyclines.

Instances of esophageal ulcerations have been reported in patients receiving oral tetracyclines. Most of the patients were reported to have taken the medication immediately before lying down. (See .) DOSAGE AND ADMINISTRATION

Skin: Maculopapular and erythematous rashes, erythema multiforme. Exfoliative dermatitis has been reported but is uncommon. Fixed drug eruptions and Stevens-Johnson syndrome have been reported rarely. Lesions occurring on the glans penis have caused balanitis. Pigmentation of the skin and mucous membranes has also been reported. Photosensitivity is discussed above. (See .) WARNINGS

Renal toxicity: Acute renal failure. Rise in BUN has been reported and is apparently dose related. Nephrogenic diabetes insipidus. (See .) WARNINGS

Hypersensitivity reactions: Urticaria, angioneurotic edema, polyarthralgia, anaphylaxis, anaphylactoid purpura, pericarditis, exacerbation of systemic lupus erythematosus, lupus-like syndrome, pulmonary infiltrates with eosinophilia.

Hematologic: Hemolytic anemia, thrombocytopenia, neutropenia and eosinophilia have been reported.

CNS: Pseudotumor cerebri (benign intracranial hypertension) in adults and bulging fontanels in infants (see). Dizziness, headache, tinnitus, and visual disturbances have been reported. Myasthenic syndrome has been reported rarely. PRECAUTIONS-General

Other: When given over prolonged periods, tetracyclines have been reported to produce brown-black microscopic discoloration of thyroid glands. No abnormalities of thyroid function studies are known to occur. Very rare cases of abnormal thyroid function have been reported.

Tooth discoloration has occurred in pediatric patients less than 8 years of age (see), and also has been reported rarely in adults. WARNINGS

OVERDOSAGE

In case of overdosage, discontinue medication, treat symptomatically and institute supportive measures. Tetracyclines are not removed in significant quantities by hemodialysis or peritoneal dialysis.

DOSAGE & ADMINISTRATION

Therapy should be continued for at least 24 to 48 hours after symptoms and fever have subsided.

Concomitant therapy: Absorption of tetracyclines is impaired by antacids containing aluminum, calcium, or magnesium, and by iron-containing preparations. Foods and some dairy products also interfere with absorption. Oral forms of tetracycline should be given at least 1 hour before or 2 hours after meals.

In patients with renal impairment: (See .) Tetracyclines should be used cautiously in patients with impaired renal function. Total dosage should be decreased by reduction of recommended individual doses and/or by extending time intervals between doses. WARNINGS

In patients with liver impairment: Tetracyclines should be used cautiously in patients with impaired liver function. Total dosage should be decreased by reduction of recommended individual doses and/or by extending time intervals between doses.

Administration of adequate amounts of fluid with the oral formulations of tetracyclines is recommended to wash down the drugs and reduce the risk of esophageal irritation and ulceration. (See .) ADVERSE REACTIONS

Adults: Usual daily dose - Four divided doses of 150 mg each or two divided doses of 300 mg each.

For pediatric patients above eight years of age: Usual daily dose, 7 to 13 mg per kg body weight per day, depending upon the severity of the disease, divided into two to four doses not to exceed adult dosage of 600 mg per day.

Gonorrhea patients sensitive to penicillin may be treated with demeclocycline administered as an initial oral dose of 600 mg followed by 300 mg every 12 hours for four days to a total of 3 grams.

HOW SUPPLIED

NDC:68151-0155-1 in a PACKAGE of 1 TABLETS